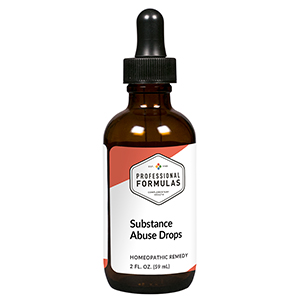 DRUG LABEL: Substance Abuse Drops
NDC: 63083-2063 | Form: LIQUID
Manufacturer: Professional Complementary Health Formulas
Category: homeopathic | Type: HUMAN OTC DRUG LABEL
Date: 20190815

ACTIVE INGREDIENTS: AVENA SATIVA FLOWERING TOP 2 [hp_X]/59 mL; VALERIAN 2 [hp_X]/59 mL; APOCYNUM CANNABINUM ROOT 3 [hp_X]/59 mL; NUTMEG 3 [hp_X]/59 mL; COFFEA ARABICA SEED, ROASTED 3 [hp_X]/59 mL; STRYCHNOS NUX-VOMICA SEED 3 [hp_X]/59 mL; TOBACCO LEAF 4 [hp_X]/59 mL; WORMWOOD 6 [hp_X]/59 mL; ANTIMONY POTASSIUM TARTRATE 6 [hp_X]/59 mL; GOLD 6 [hp_X]/59 mL; HYOSCYAMUS NIGER 60 [hp_X]/59 mL; GONORRHEAL URETHRAL SECRETION HUMAN 60 [hp_X]/59 mL; SUCROSE 60 [hp_X]/59 mL; BETA-ENDORPHIN HUMAN 8 [hp_X]/59 mL
INACTIVE INGREDIENTS: ALCOHOL; WATER

C63

ACTIVE INGREDIENTS

Avena sativa 2X
Valeriana officinalis 2X
Apocynum cannabinum 3X
Nux moschata 3X
Coffea tosta 3X, 12X, 60X, 100X
Nux vomica 3X, 12X, 60X, 100X
Tabacum 4X, 12X, 60X, 100X
Absinthium 6X
Antimonium tartaricum 6X
Aurum metallicum 6X, 12X, 30X
Hyoscyamus niger 60X
Medorrhinum 60X
Sucrose 60X
Endorphins 8X, 12X, 60X, 100X

QUESTIONS

Professional Formulas

PO Box 2034 Lake Oswego, OR 97035

INDICATIONS

For the temporary relief of irritability, reduced motivation, cravings, or inability to concentrate due to overindulgence of food or other dietary substances.*

PURPOSE

*Claims based on traditional homeopathic practice, not accepted medical evidence. Not FDA evaluated.

WARNINGS

In case of overdose, get medical help or contact a poison control center right away.

Keep out of the reach of children.

PREGNANCY OR BREAST FEEDING

If pregnant or breastfeeding, ask a healthcare professional before use.

DIRECTIONS

Place drops under tongue 30 minutes before/after meals. Adults and children 12 years and over: Take 10 drops up to 3 times per day. Consult a physician for use in children under 12 years of age.

OTHER INFORMATION

Tamper resistant. If seal is broken, do not use. After opening, close container tightly and store at room temperature away from heat.

INACTIVE INGREDIENTS

20% ethanol, purified water.

LABEL

Est 1985

Professional Formulas

Complementary Health

Substance Abuse Drops

Homeopathic Remedy

2 FL. OZ. (59 mL)